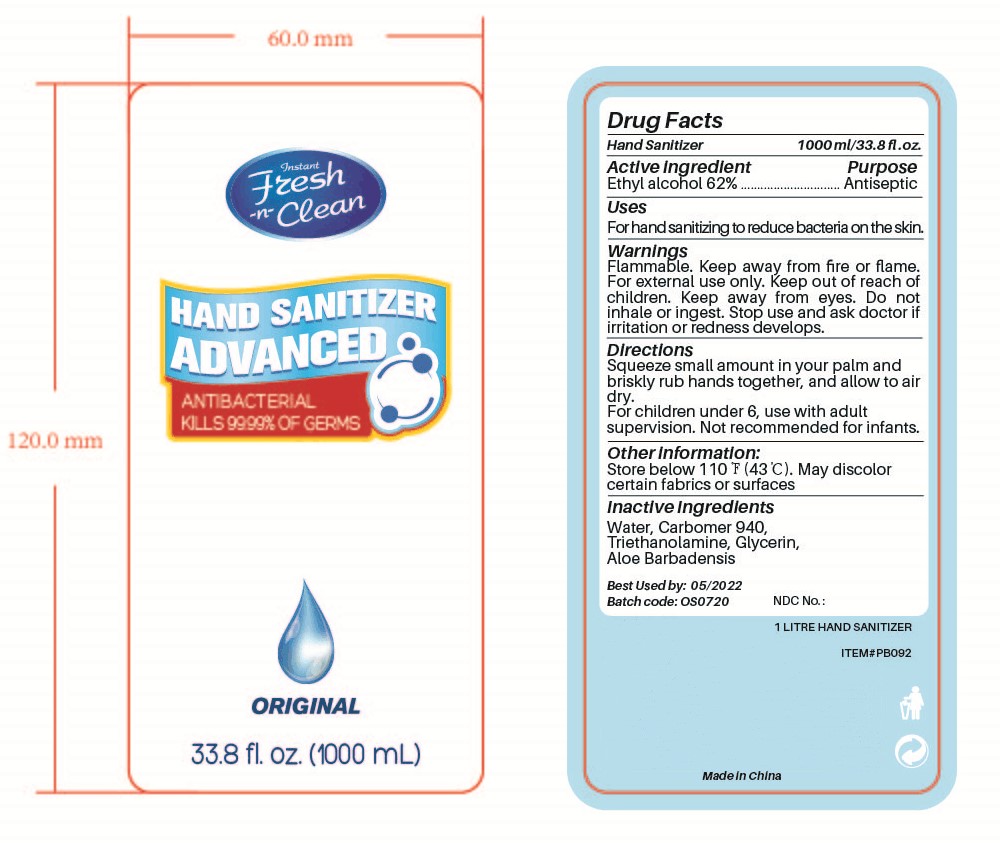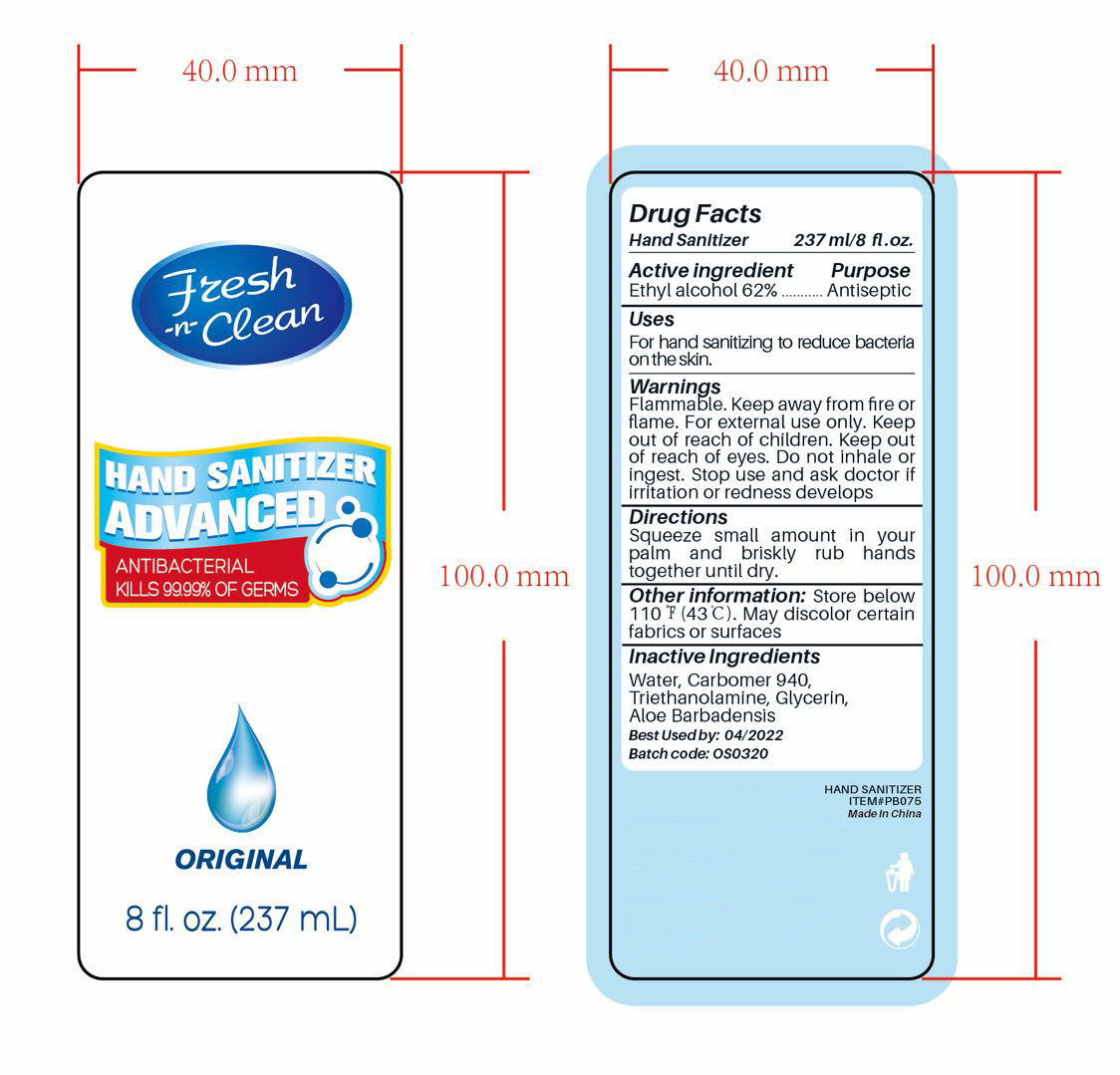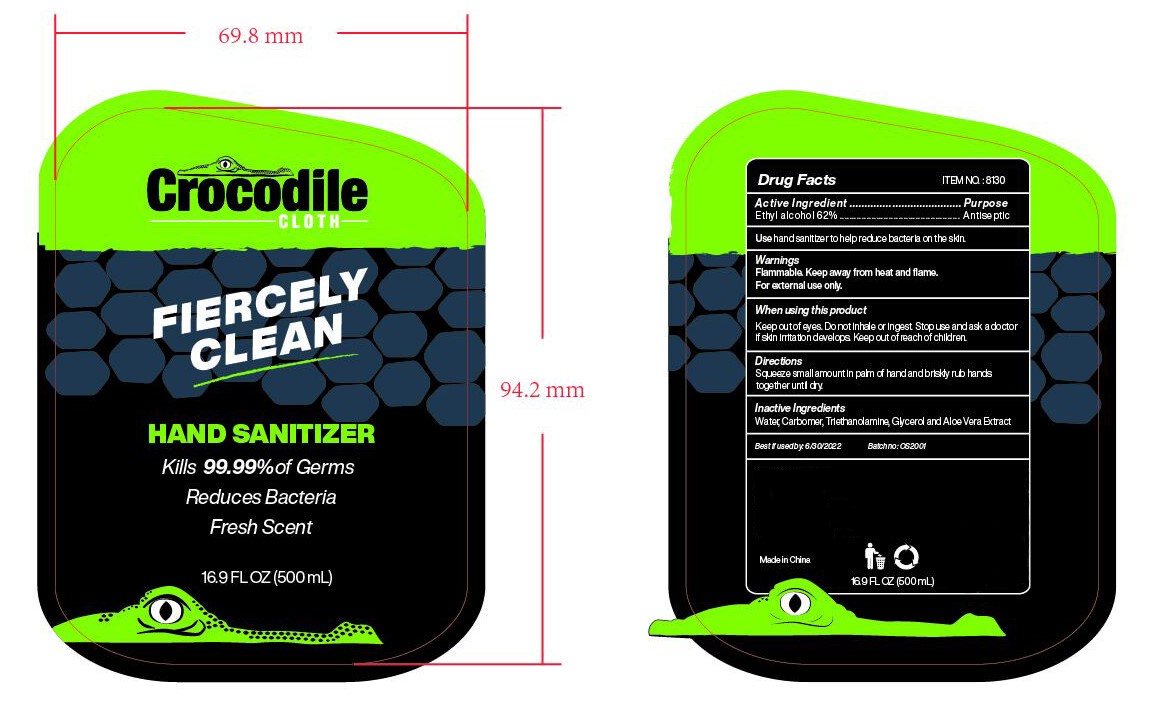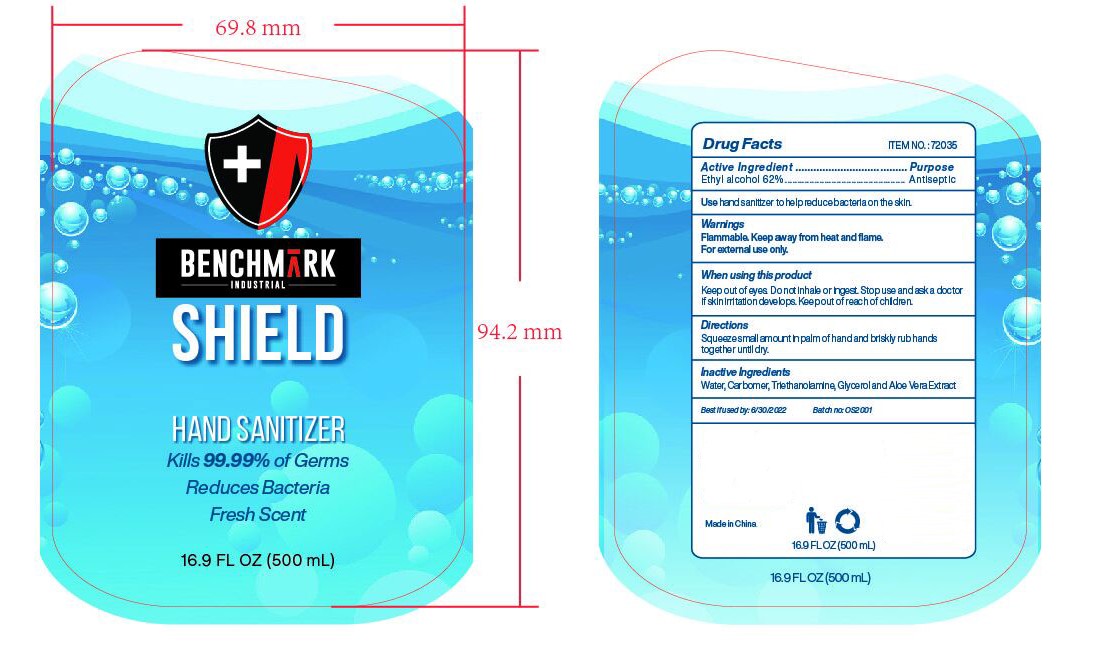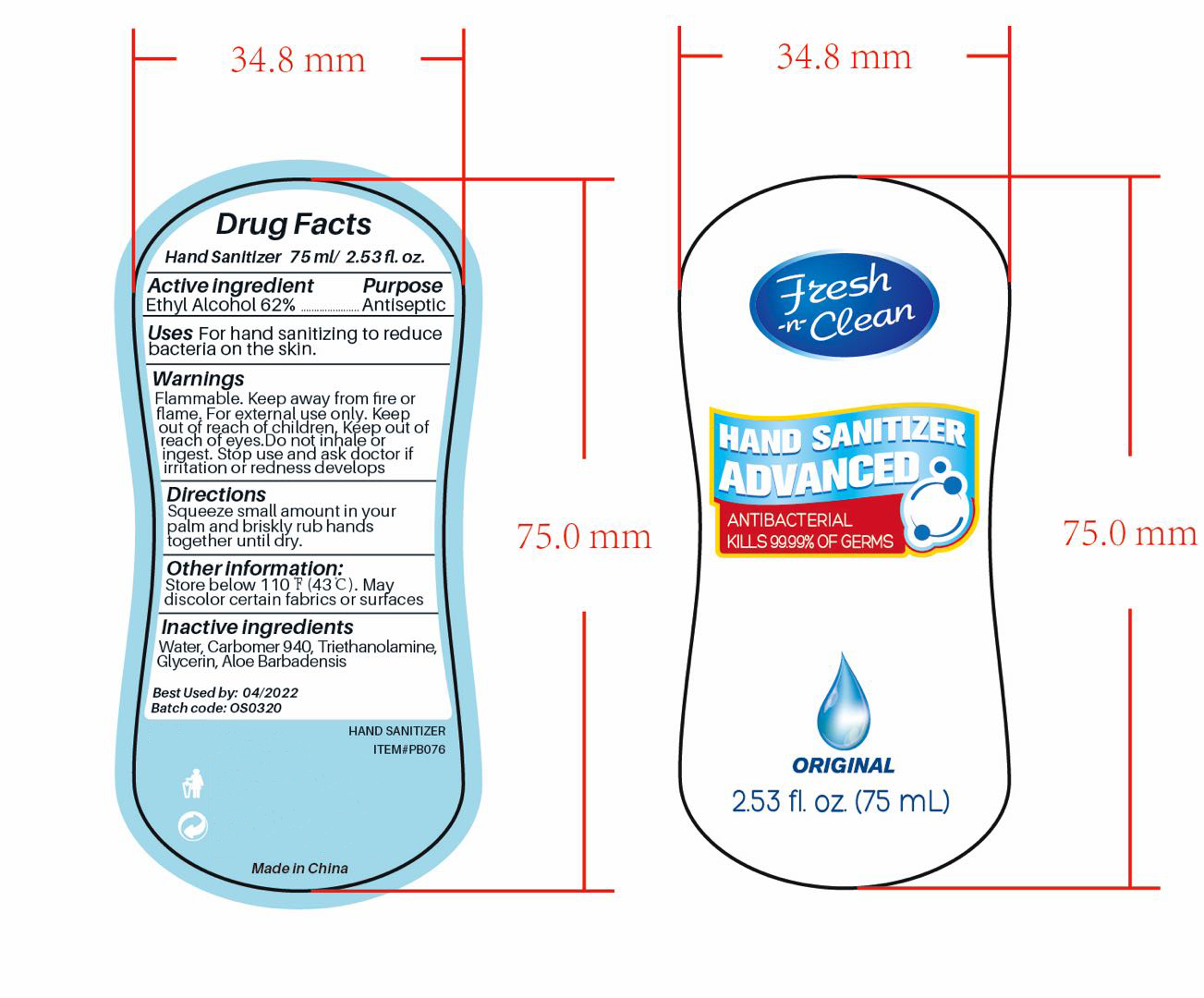 DRUG LABEL: HAND SANITIZER
NDC: 47993-211 | Form: GEL
Manufacturer: NINGBO JIANGBEI OCEAN STAR TRADING CO.,LTD
Category: otc | Type: HUMAN OTC DRUG LABEL
Date: 20201118

ACTIVE INGREDIENTS: ALCOHOL 62 g/112 mL
INACTIVE INGREDIENTS: ALOE VERA LEAF 1 g/112 mL; GLYCERIN 2 g/112 mL; WATER 20 g/112 mL; CARBOMER 940 12 g/112 mL; TRIETHANOLAMINE BENZOATE 3 g/112 mL

47993-211

Active ingredients

Ethyl Alcohol 62%

PURPOSE

Antiseptic

Uses:
For hand sanitizing to reduce bacteria on the skin.

Uses:

For hand sanitizing to reduce bacteria on the skin.

Warnings:

Flammable. Keep away from fire or flame. For external use only. Keep away from eyes. Do not inhale or ingest.

Stop use and ask doctor if irritation or redness develops

Directions:

Squeeze small amount in your palm and briskly rub hands together, and allow to air dry.

Directions:

Squeeze small amount in your palm and briskly rub hands together, and allow to air dry.

Keep out of reach of children.

Other Information

Store below 110F(43C). May discolor certain fabrics or surfaces.

Inactive ingredients

Water，Carbomer 940，Triethanolamine，Glycerin，Aloe Barbadensis